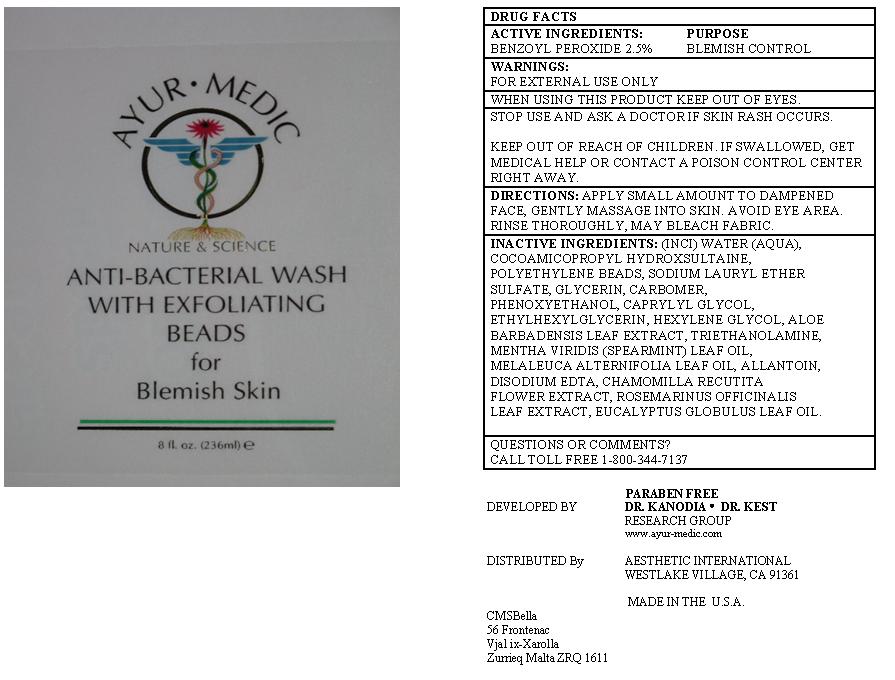 DRUG LABEL: Anti-Bacterial Wash with Exfoliating Beads for Blemish skin
NDC: 62742-4058 | Form: GEL
Manufacturer: Allure Labs, Inc.
Category: otc | Type: HUMAN OTC DRUG LABEL
Date: 20100915

ACTIVE INGREDIENTS: BENZOYL PEROXIDE 25 mg/1 mL

DRUG FACTS

ACTIVE INGREDIENTS:

Benzoyl Peroxide 2.5%

PURPOSE:

Blemish Control

WARNINGS:

For external use only

When using this product keep out of eyes.

Stop use and ask a doctor if skin rash occurs.

Keep out of reach of children. If swallowed, get medical help or contact a poison a poison control center right away.

DIRECTIONS:

Apply small amount to dampened face, gently massage into skin, avoid eye area, rinse thoroughly.

May bleach fabric.

INACTIVE INGREDIENTS:

(INCI) Water (Aqua), Cocoamidopropyl Hydroxsultaine, Polyethylene beads, Sodium Lauryl Ether Sulfate, Glycerin, Carbomer, Phenoxyethanol, Caprylyl Glycol, Ethylhexylglycerin, Hexylene Glycol, Aloe barbedensis Leaf Extract, Triethanolamine, Mentha viridis (Spearmint) leaf oil, Melaleuca alternifolia leaf oil, Allantoin, Disodium EDTA, Chamomilla recutita flower extract, Rosemarinus officinalis leaf extract, Eucalyptus globulus leaf oil.

PACKAGE LABEL

QUESTION OR COMMENTS?
CALL TOLL FREE 1-800-344-7137
PARABEN FREE
DEVELOPED BY: DR. KANODIA . DR. KIST
RESEARCH GROUP
www.ayru-medic.com
DISTRIBUTED BY: AESTHETIC INTERNATIONAL
WESTLAKE VILLAGE, CA 91361
MADE IN THE U.S.A
CMSBella
56 Frontenac
Vjal ix-Xarolla
Zurrieq Malta ZRQ 1611
IMAGE OF THE LABEL:
AYUR.MEDIC
ANTI-BACTERIAL WASH WITH EXFOLIATING BEADS FOR Blemish Skin
8 fl. oz. (236ml)

INDICATIONS AND USAGE

Anti-bacterial Wash with Exfoliating Beads for Blemish Skin